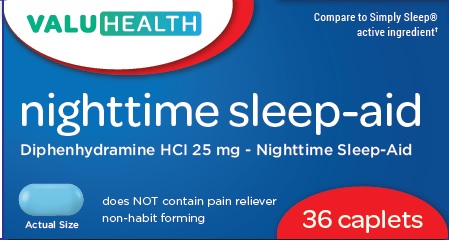 DRUG LABEL: NIGHTTIME SLEEP AID
NDC: 68210-4132 | Form: TABLET
Manufacturer: SPIRIT PHARMACEUTICALS LLC
Category: otc | Type: HUMAN OTC DRUG LABEL
Date: 20241213

ACTIVE INGREDIENTS: DIPHENHYDRAMINE HYDROCHLORIDE 25 mg/1 1
INACTIVE INGREDIENTS: SILICON DIOXIDE; CROSCARMELLOSE SODIUM; ANHYDROUS DIBASIC CALCIUM PHOSPHATE; FD&C BLUE NO. 1; FD&C BLUE NO. 2; LECITHIN, SOYBEAN; MAGNESIUM STEARATE; MICROCRYSTALLINE CELLULOSE; POLYETHYLENE GLYCOL, UNSPECIFIED; POLYVINYL ALCOHOL, UNSPECIFIED; TALC; TITANIUM DIOXIDE

NIGHTTIME SLEEP AID CAPLETS

Drug Facts

Active ingredients (in each caplet)

Diphenhydramine HCl 25mg

Purpose

nighttime sleep-aid

Uses

for the relief of occasional sleeplessness

Warnings

Do not use

- for children under 12 years of age
- with any other product containing diphenhydramine, even one used on skin

Ask a doctor before use if you have

- a breathing problem such as emphysema or chronic bronchitis
- glaucoma
- trouble urinating due to an enlarged prostate gland

Ask a doctor or pharmacist before use if you are taking sedatives or tranquilizers

When using this product

- avoid alcoholic drinks
- drowsiness will occur
- do not drive a motor vehicle or operate machinery

Stop use and ask a doctor if

sleeplessness persists continuously for more than 2 weeks. Insomnia may be a symptom of serious underlying medical illness.

PREGNANCY OR BREAST FEEDING

If pregnant or breast-feeding, ask a health professional before use.

Keep out of reach of children.

Overdose warning

In case of overdose, get medical help or contact a Poison Control Center right away. (1-800-222-1222)

Directions

adults and children 12 years and over | take 2 caplets at bedtime if needed, or as directed by a doctor
children under 12 years | do not use

Other information

each caplet contains: calcium 25 mg

store between 20-25°C(68-77°F). Avoid high humidity. Protect from light.

Inactive ingredients

Colloidal siicon dioxide, croscarmellose sodium, dicalcium phosphate, FD&C Blue#1, FD&C Blue#2, lecithin, magnesium stearate, microcrystalline cellulose, polyethylene glycol, polyvinyl alcohol, talc, titanium dioxide

Questions or comments?

1-888-333-9792

PRINCIPLA DISPLAY PANEL

Nighttime sleep-aid
Diphenhydramine HCI 25 mg - Nighttime Sleep-Aid
Does NOT contain pain reliever
Non-habit forming
36 Caplets